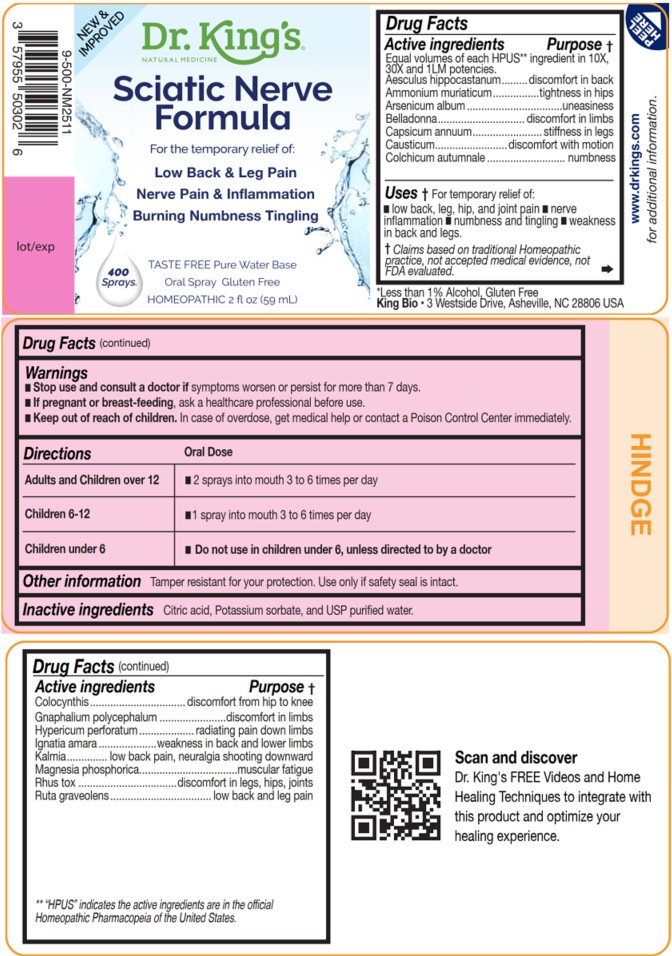 DRUG LABEL: Sciatic Nerve Formula
NDC: 57955-9988 | Form: LIQUID
Manufacturer: King Bio Inc.
Category: homeopathic | Type: HUMAN OTC DRUG LABEL
Date: 20251020

ACTIVE INGREDIENTS: HORSE CHESTNUT 10 [hp_X]/59 mL; AMMONIUM CHLORIDE 10 [hp_X]/59 mL; ARSENIC TRIOXIDE 10 [hp_X]/59 mL; ATROPA BELLADONNA 10 [hp_X]/59 mL; CAPSICUM 10 [hp_X]/59 mL; CAUSTICUM 10 [hp_X]/59 mL; COLCHICUM AUTUMNALE BULB 10 [hp_X]/59 mL; CITRULLUS COLOCYNTHIS FRUIT PULP 10 [hp_X]/59 mL; PSEUDOGNAPHALIUM OBTUSIFOLIUM WHOLE 10 [hp_X]/59 mL; HYPERICUM PERFORATUM WHOLE 10 [hp_X]/59 mL; STRYCHNOS IGNATII SEED 10 [hp_X]/59 mL; KALMIA LATIFOLIA LEAF 10 [hp_X]/59 mL; MAGNESIUM PHOSPHATE, DIBASIC TRIHYDRATE 10 [hp_X]/59 mL; TOXICODENDRON PUBESCENS LEAF 10 [hp_X]/59 mL; RUTA GRAVEOLENS FLOWERING TOP 10 [hp_X]/59 mL
INACTIVE INGREDIENTS: ANHYDROUS CITRIC ACID; POTASSIUM SORBATE; WATER

Sciatic Nerve Formula

Active ingredients

Equal volumes of each HPUS** ingredient in 10X,
30X and 1LM potencies.

Aesculus hippocastanum, Ammonium muriaticum, Arsenicum album, Belladonna, Capsicum annuum, Causticum, Colchicum autumnale, Colocynthis, Gnaphalium polycephalum, Hypericum perforatum, Ignatia amara, Kalmia, Magnesia phosphorica, Rhus tox and Ruta graveolens.

**“HPUS” indicates the active ingredients are in the official Homeopathic
Pharmacopeia of the United States.

INDICATIONS AND USAGE

Uses † for temporary relief of:

- low back, leg, hip, and joint pain
- nerve inflammation
- numbness and tingling
- weakness in back and legs

† Claims based on traditional Homeopathic practice, not accepted medical evidence, not
FDA evaluated.

Questions

Sciatic Nerve Formula

Taste free, Pure Water Base

Oral Spray Gluten Free

HOMEOPATHIC 2 fl oz (59 mL)

*Less than 1% Alcohol

King Bio • 3 Westside Drive, Asheville, NC 28806 USA

Scan and discover

Dr. King's FREE Videos and Home
Healing Techniques to integrate with
this product and optimize your
healing experience.

www.DrKings.com
for additional information.

Warnings

- Stop use and consult a doctor if symptoms worsen or persist for more than 7 days.
- If pregnant or breast-feeding, ask a healthcare professional before use.

- Keep out of reach of children. In case of overdose, get medical help or contact a Poison Control Center immediately.

DOSAGE AND ADMINISTRATION

Directions | Oral Dose
Adults and Children over 12 | - 2 sprays into mouth 3 to 6 times per day
Children 6-12 | - 1 spray into mouth 3 to 6 times per day
Children under 6 | - Do not use in children under 6, unless directed to by a doctor

Other information

Tamper resistant for your protection. Use only if safety seal is intact.

Inactive Ingredients

Citric Acid, and Potassium Sorbate, and USP Purified Water.

PURPOSE

Equal volumes of each HPUS ingredient in 10X, 30X, and 1LM
potencies.

Active ingredients Purpose †

Aesculus hippocastanum.......................discomfort in back
Ammonium muriaticum...........................tightness in hips
Arsenicum album ..........................................uneasiness
Belladonna.........................................discomfort in limbs
Capsicum annuum...................................stiffness in legs
Causticum....................................discomfort with motion
Colchicum autumnale .....................................numbness

Colocynthis............................discomfort from hip to knee
Gnaphalium polycephalum ...................discomfort in limbs
Hypericum perforatum ...............radiating pain down limbs
Ignatia amara ................weakness in back and lower limbs
Kalmia.............low back pain, neuralgia shooting downward
Magnesia phosphorica..............................muscular fatigue
Rhus tox .............................discomfort in legs, hips, joints
Ruta graveolens................................low back and leg pain

**“HPUS” indicates the active ingredients are in the official Homeopathic
Pharmacopeia of the United States.

† Claims based on traditional Homeopathic practice, not accepted medical evidence, not
FDA evaluated.